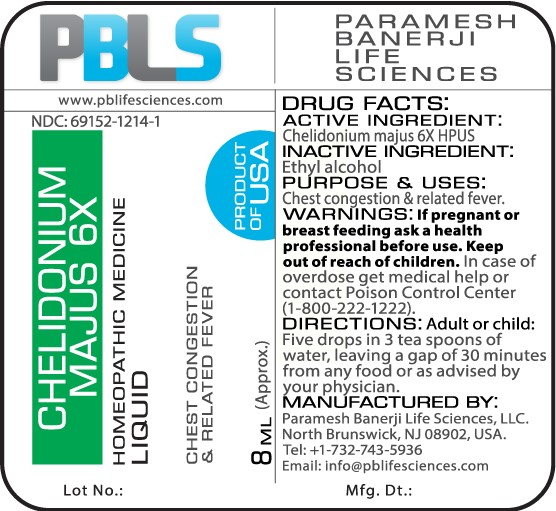 DRUG LABEL: Chelidonium majus 6X
NDC: 69152-1214 | Form: LIQUID
Manufacturer: Paramesh Banerji Life Sciences LLC
Category: homeopathic | Type: HUMAN OTC DRUG LABEL
Date: 20170310

ACTIVE INGREDIENTS: CHELIDONIUM MAJUS 6 [hp_X]/8 mL
INACTIVE INGREDIENTS: ALCOHOL

DRUG FACTS: Active Ingredient

Chelidonium majus 6X HPUS

Inactive Ingredient

Ethyl alcohol

Purpose

Chest congestion & related fever

Uses

Chest congestion & related fever

Warnings

If pregnant or breast feeding ask a health professional before use.

Keep out of reach of children. In case of overdose, get medical help or contact a Poison Control Center (1-800-222-1222) right away.

Direction

Adult or child: Five drops in 3 tea spoons of water, leaving a gap of 30 minutes from any food or as advised by your physician.

Manufactured by

Paramesh Banerji Life Sciences, LLC.

North Brunswick, NJ 08902, USA.

Tel: +1-732-743-5936

Email: info@pblifesciences.com

Principal Display Panel

NDC: 69152-1214-1

Chelidonium majus 6X

Homeopathic Medicine

Liquid

Chest congestion & related fever

8 mL (Approx.)

Product of USA